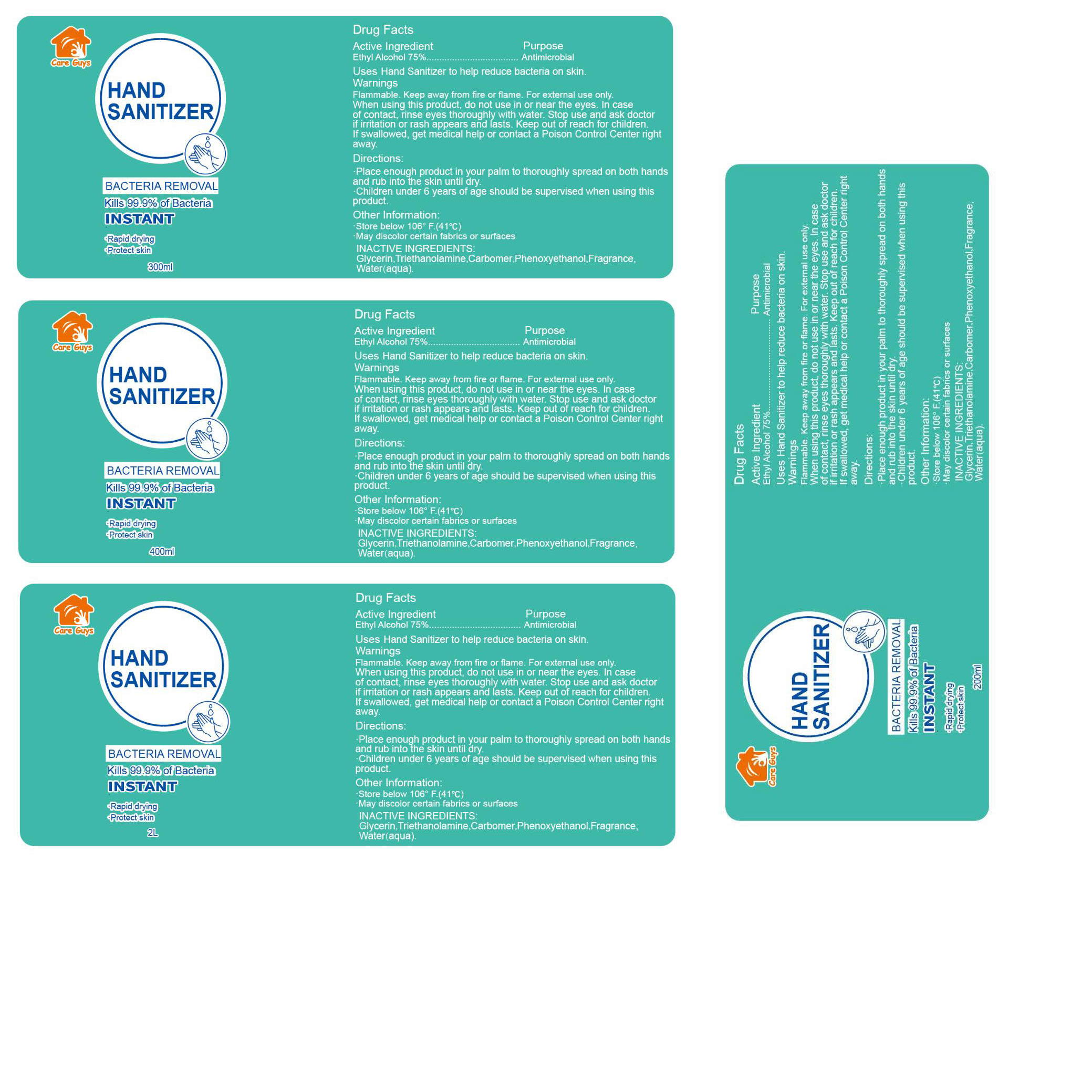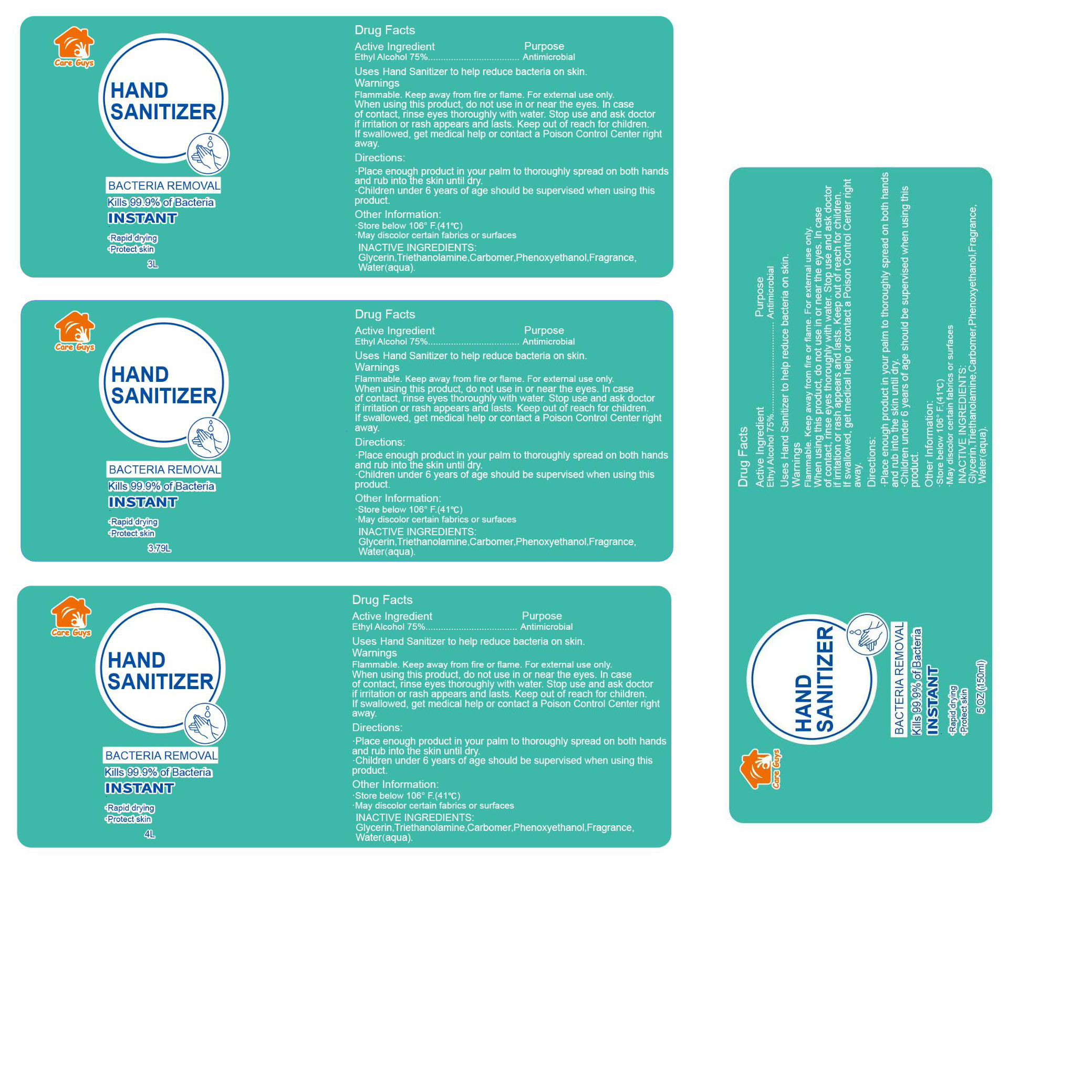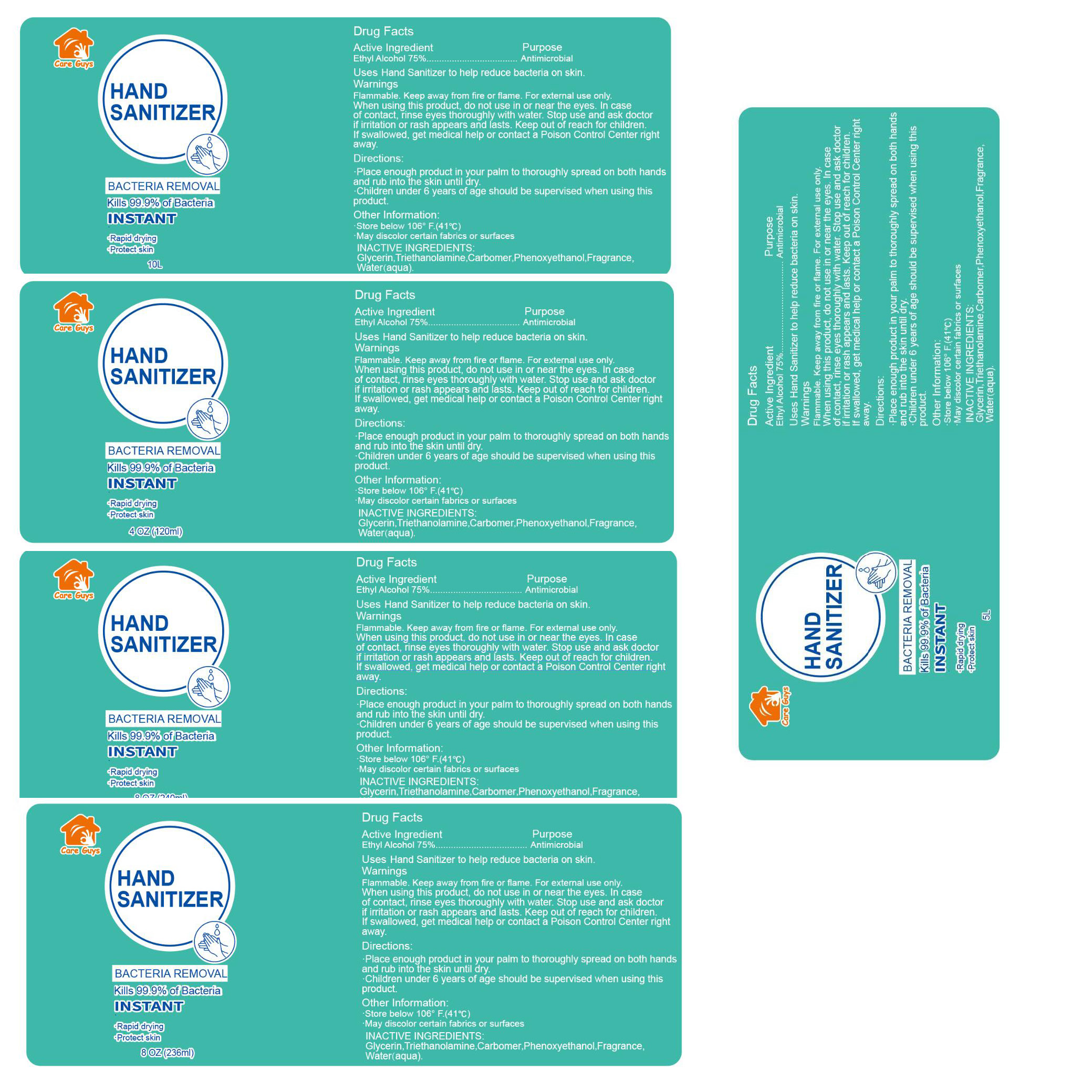 DRUG LABEL: Hand sanitizer
NDC: 75126-011 | Form: GEL
Manufacturer: Jiangyin Yinghuameng Houseware Co., Ltd.
Category: otc | Type: HUMAN OTC DRUG LABEL
Date: 20200713

ACTIVE INGREDIENTS: ALCOHOL 75 mL/100 mL
INACTIVE INGREDIENTS: CARBOMER HOMOPOLYMER, UNSPECIFIED TYPE; GLYCERIN; TROLAMINE; PHENOXYETHANOL; WATER

HAND SANITIZER

Active Ingredient

Ethyl Alcohol 75%.

Purpose

Antimicrobial

Uses

Hand Sanitizer to help reduce

bacteria on skin.

Warnings

Flammable.Keep away from fire or flame.

For external use only.

When using this product

do not use in or near the eyes.In case of contact,rinse eyes thoroughly with water.Stop use and

ask doctor if irritation or rash appears and lasts.Keep out of reach for children.

If swallowed,get medical help or contact a Poison Control Center right away.

Directions

Place enough Product in your palm to thoroughly spread on both handsand rub into the skin until dry.

Children under 6 years of age should be supervised when using this product.

Other Information

Store below 106°F.(41℃)

May discolor certain fabrics or surfaces

INACTIVE INGREDIENTS

Glycerin, Triethanolamine, Carbomer,Phenoxyethanol,Fragrance,Water(aqua)